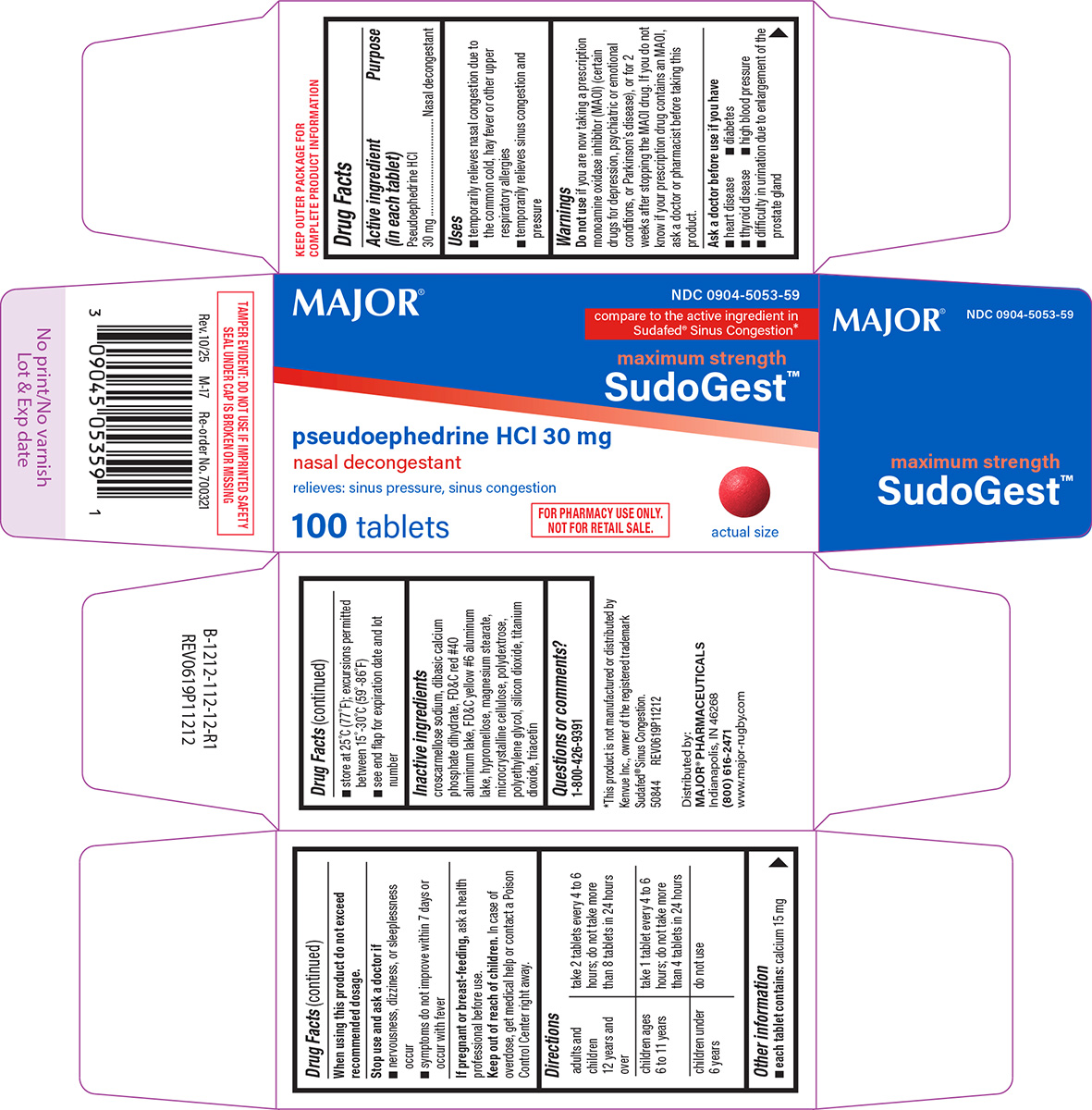 DRUG LABEL: SudoGest
NDC: 0904-5053 | Form: TABLET, FILM COATED
Manufacturer: Major Pharmaceuticals
Category: otc | Type: HUMAN OTC DRUG LABEL
Date: 20251021

ACTIVE INGREDIENTS: PSEUDOEPHEDRINE HYDROCHLORIDE 30 mg/1 1
INACTIVE INGREDIENTS: CROSCARMELLOSE SODIUM; DIBASIC CALCIUM PHOSPHATE DIHYDRATE; FD&C RED NO. 40 ALUMINUM LAKE; FD&C YELLOW NO. 6 ALUMINUM LAKE; HYPROMELLOSE, UNSPECIFIED; MAGNESIUM STEARATE; MICROCRYSTALLINE CELLULOSE; POLYDEXTROSE; POLYETHYLENE GLYCOL, UNSPECIFIED; SILICON DIOXIDE; TITANIUM DIOXIDE; TRIACETIN

Major 44-112

Active ingredient (in each tablet)

Pseudoephedrine HCl 30 mg

Purpose

Nasal decongestant

Uses

- temporarily relieves nasal congestion due to the common cold, hay fever or other upper respiratory allergies
- temporarily relieves sinus congestion and pressure

Warnings

Do not use

if you are now taking a prescription monoamine oxidase inhibitor (MAOI) (certain drugs for depression, psychiatric or emotional conditions, or Parkinson's disease), or for 2 weeks after stopping the MAOI drug. If you do not know if your prescription drug contains an MAOI, ask a doctor or pharmacist before taking this product.

Ask a doctor before use if you have

- heart disease
- diabetes
- thyroid disease
- high blood pressure
- difficulty in urination due to enlargement of the prostate gland

When using this product

do not exceed recommended dosage.

Stop use and ask a doctor if

- nervousness, dizziness, or sleeplessness occur
- symptoms do not improve within 7 days or occur with fever

If pregnant or breast-feeding,

ask a health professional before use.

Keep out of reach of children.

In case of overdose, get medical help or contact a Poison Control Center right away.

Directions

adults and children 12 years and over | take 2 tablets every 4 to 6 hours; do not take more than 8 tablets in 24 hours
children ages 6 to 11 years | take 1 tablet every 4 to 6 hours; do not take more than 4 tablets in 24 hours
children under 6 years | do not use

Other information

- each tablet contains: calcium 15 mg
- store at 25°C (77°F); excursions permitted between 15°-30°C (59°-86°F)
- see end flap for expiration date and lot number

Inactive ingredients

croscarmellose sodium, dibasic calcium phosphate dihydrate, FD&C red #40 aluminum lake, FD&C yellow #6 aluminum lake, hypromellose, magnesium stearate, microcrystalline cellulose, polydextrose, polyethylene glycol, silicon dioxide, titanium dioxide, triacetin

Questions or comments?

1-800-426-9391

Principal Display Panel

NDC 0904-5053-59

MAJOR®

compare to the active ingredient in
Sudafed® Sinus Congestion*

maximum strength
SudoGest™

pseudoephedrine HCl 30 mg
nasal decongestant
relieves: sinus pressure, sinus congestion

100 tablets

FOR PHARMACY USE ONLY.
NOT FOR RETAIL SALE.

actual size

TAMPER EVIDENT: DO NOT USE IF IMPRINTED SAFETY
SEAL UNDER CAP IS BROKEN OR MISSING

Rev. 10/25 M-17 Re-order No. 700321

*This product is not manufactured or distributed by
Kenvue Inc., owner of the registered trademark
Sudafed® Sinus Congestion.

50844 REV0619P11212

Distributed by:
MAJOR® PHARMACEUTICALS
Indianapolis, IN 46268
(800) 616-2471
www.major-rugby.com

Major 44-112